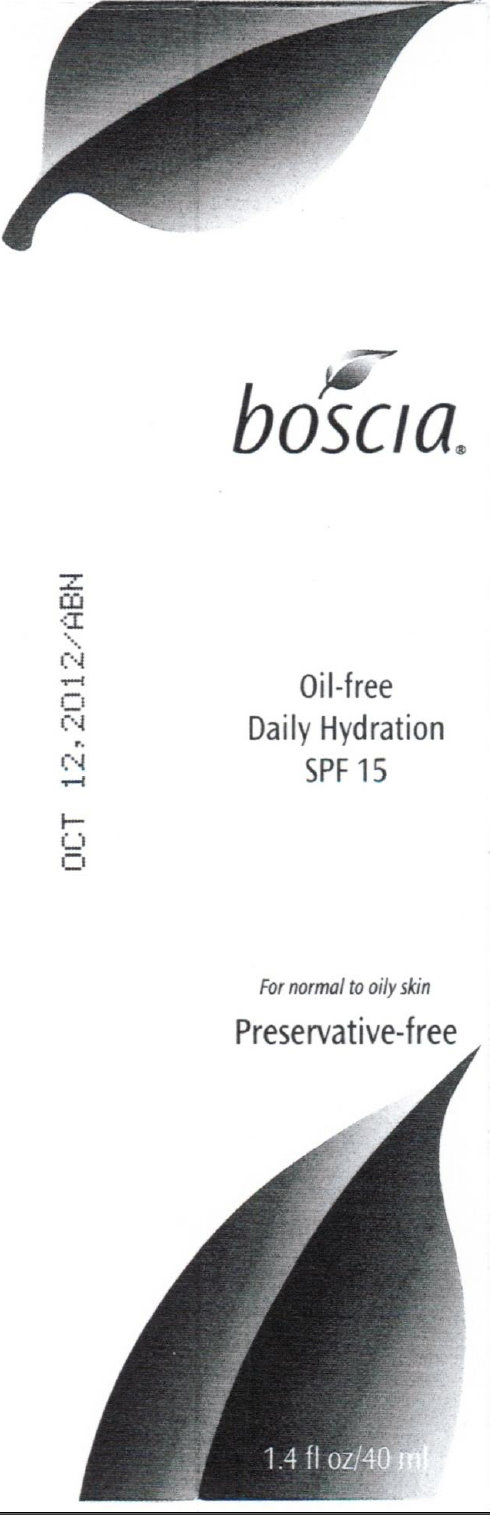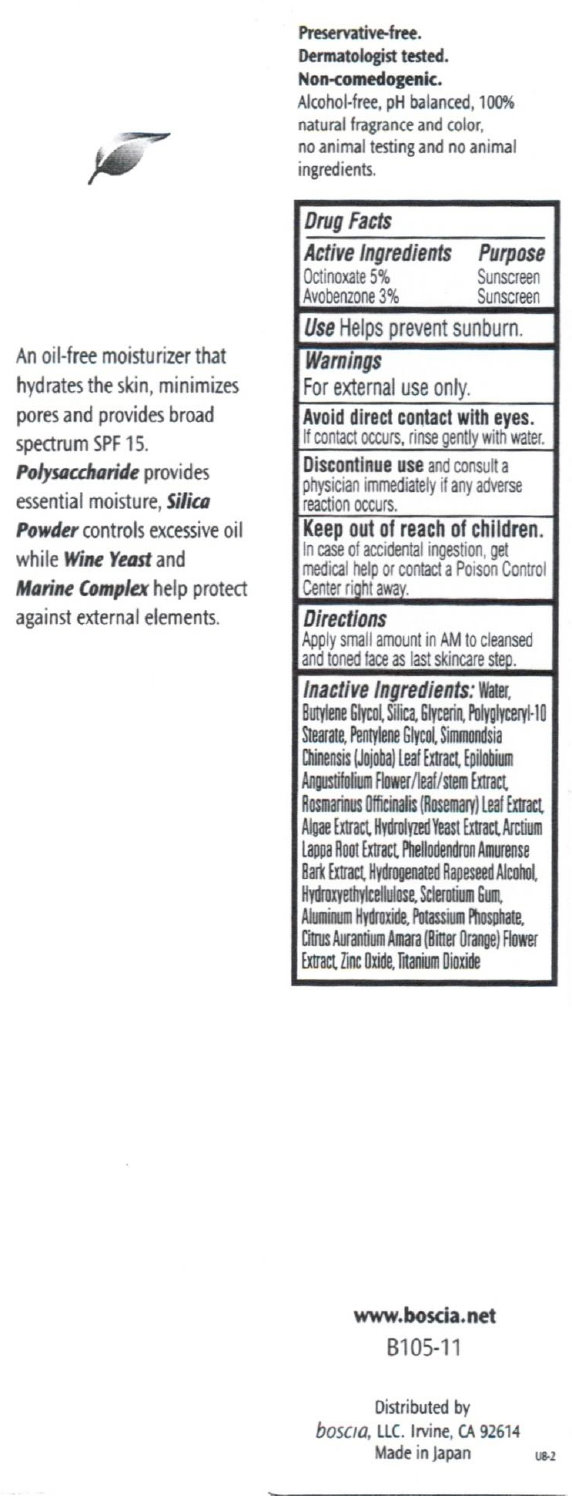 DRUG LABEL: Oil-Free Daily Hydration SPF 15
NDC: 76151-105 | Form: CREAM
Manufacturer: Boscia LLC
Category: otc | Type: HUMAN OTC DRUG LABEL
Date: 20250131

ACTIVE INGREDIENTS: OCTINOXATE 50 mg/1 mL; AVOBENZONE 30 mg/1 mL
INACTIVE INGREDIENTS: WATER; BUTYLENE GLYCOL; SILICON DIOXIDE; GLYCERIN; PENTYLENE GLYCOL; EPILOBIUM ANGUSTIFOLIUM FLOWERING TOP; ROSEMARY; ARCTIUM LAPPA ROOT; PHELLODENDRON AMURENSE BARK; HYDROXYETHYL CELLULOSE (140 CPS AT 5%); ALUMINUM HYDROXIDE; POTASSIUM PHOSPHATE; CITRUS AURANTIUM FLOWER; ZINC OXIDE; TITANIUM DIOXIDE

Oil-Free Daily Hydration SPF 15

ACTIVE INGREDIENT

Active Ingredients Purpose Octinoxate 5% Sunscreen Avobenzone 3% Sunscreen

PURPOSE

Use Helps prevent sunburn.

Use

Helps prevent sunburn.

Warnings For external use only.

WHEN USING

Avoid direct contact with eyes. If contact occurs, rinse gently with water.

STOP USE

Discontinue use and consult a physician immediately if any adverse reaction occurs.

Keep out of reach of children.

OTHER SAFETY INFORMATION

In case of accidental ingestion, get medical help or contact a Poison Control Center right away.

DOSAGE AND ADMINISTRATION

Directions Apply small amount in AM to cleansed and toned face as last skincare step.

INACTIVE INGREDIENT

Inactive Ingredients: Water, Butylene Glycol, Silica, Glycerin, Polyglyceryl-10 Stearate, Pentylene Glycol, Simmondsia Chinensis (Jojoba) Leaf Extract, Epilobium Angustifolium Flower/leaf/stem Extract, Rosmarinus Officinalis (Rosemary) Leaf Extract, Algae Extract, Hydrolyzed Yeast Extract, Arctium Lappa Root Extract, Phellodendron Amurense Bark Extract, Hydrogenated Rapeseed Alcohol, Hydroxyethylcellulose, Sclerotium Gum, Aluminum Hydroxide, Potassium Phosphate, Citrus Aurantium Amara (Bitter Orange) Flower Extract, Zinc Oxide, Titanium Dioxide.

DESCRIPTION

Preservative-free. Dermatologist tested. Non-comedogenic. Alcohol-free, pH balanced, 100% natural fragrance and color, no animals testing and no animal ingredients. An oil-free moisturizer that hydrates the skin, minimizes pores and providers broad spectrum SPF 15. Polysaccharide provides essential moisture, silica powder controls excessive oil while wine Yeast and Marine Complex help protect against external elements. www.boscia.net B105-11 Distributed by boscia LLC. Irvine, CA 92614 Made in Japan U8-2

PACKAGE LABEL

boscia Oil-free Daily Hydration SPF 15 For normal to oily skin Preservative-free 1.4 fl oz/40 ml

PACKAGE LABEL

www.boscia.net B105-11 Distributed by boscia LLC. Irvine, CA 92614 Made in Japan U8-2